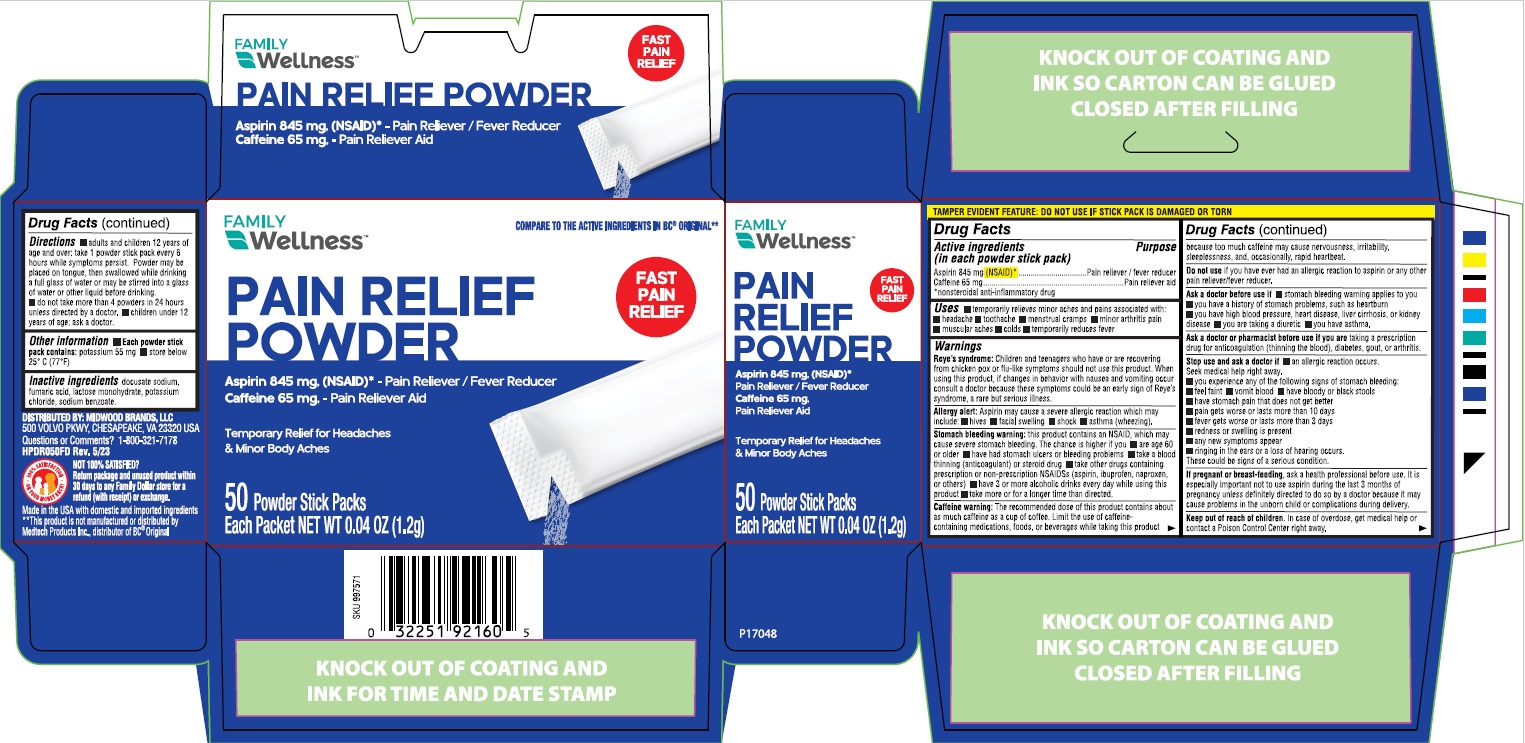 DRUG LABEL: Family Wellness Pain Relief Powder
NDC: 55319-892 | Form: POWDER
Manufacturer: Family Dollar Services Inc
Category: otc | Type: HUMAN OTC DRUG LABEL
Date: 20241218

ACTIVE INGREDIENTS: CAFFEINE 65 mg/1 1; ASPIRIN 845 mg/1 1
INACTIVE INGREDIENTS: DOCUSATE SODIUM; FUMARIC ACID; LACTOSE MONOHYDRATE; POTASSIUM CHLORIDE; SODIUM BENZOATE

Drug Facts

Drug Facts

Active ingredient

(in each powder)

Aspirin (NSAID*) 845 mg

*nonsteroidal anti-inflammatory drug

Purpose

Pain reliever/fever reducer

Active ingredient

(in each powder)

Caffeine 65 mg

Purpose

Pain reliever aid

Uses

- temporarily relieves minor aches and pains due to:
  - headache
  - toothache
  - menstrual cramps
  - muscular aches
  - minor arthritis pain
  - colds
- temporarily reduces fever

Warnings

Reye’s syndrome: Children and teenagers who have or are recovering from chicken pox or flu-like symptoms should not use this product. When using this product, if changes in behavior with nausea and vomiting occur, consult a doctor because these symptoms could be an early sign of Reye’s syndrome, a rare but serious illness.

Allergy alert: Aspirin may cause a severe allergic reaction which may include:

- hives
- facial swelling
- shock
- asthma (wheezing)

Stomach bleeding warning: This product contains an NSAID, which may cause severe stomach bleeding. The chance is higher if you

- are age 60 or older
- have had stomach ulcers or bleeding problems
- take a blood thinning (anticoagulant) or steroid drug
- take other drugs containing prescription or nonprescription NSAIDs (aspirin, ibuprofen, naproxen, or others)
- have 3 or more alcoholic drinks every day while using this product
- take more or for a longer time than directed

Caffeine warning: The recommended dose of this product contains about as much caffeine as a cup ocoffee. Limit the use of caffeine-containing medications, foods, or beverages while taking this productbecause too much caffeine may cause nervousness, irritability, sleeplessness, and, occasionally, rapid heartbeat.

Do not use

if you have ever had an allergic reaction to aspirin or any other pain reliever/fever reducer

Ask a doctor before use if

- stomach bleeding warning applies to you
- you have a history of stomach problems, such as heartburn
- you have high blood pressure, heart disease, liver cirrhosis, or kidney disease
- you are taking a diuretic
- you have asthma

Ask a doctor or pharmacist before use if you are

taking a prescription drug for diabetes, gout, or arthritis

When using this product

limit the use of caffeine-containing drugs, foods, or drinks because too much caffeine may cause nervousness, irritability, sleeplessness, and, occasionally, rapid heart beat. The recommended dose of this product contains about as much caffeine as a cup of coffee.

Stop use and ask a doctor if

- an allergic reaction occurs. Seek medical help right away.
- you experience any of the following signs of stomach bleeding:
  - feel faint
  - vomit blood
  - have bloody or black stools
  - have stomach pain that does not get better
- pain gets worse or lasts more than 10 days
- fever gets worse or lasts more than 3 days
- redness or swelling is present
- any new symptoms appear
- ringing in the ears or a loss of hearing occurs

These could be signs of a serious condition.

If pregnant or breast-feeding,

ask a health care professional before use. It is especially important not to use aspirin during the last 3 months of pregnancy unless definitely directed to do so by a doctor because it may cause problems in the unborn child or complications during delivery.

Keep out of reach of children.

In case of overdose, get medical help or contact a Poison Control Center right away.

Directions

- adults and children 12 years of age and over: take 1 powder stick pack every 6 hours, while symptoms persist. Powder may be placed on tongue, then swallowed while drinking a full glass of water or may be stirred into a glass of water or other liquid before drinking.
- do not take more than 4 powders in 24 hours unless directed by a doctor.
- children under 12 years of age: ask a doctor.

Other information

- each powder stick pack contains: potassium 55 mg
- store below 25ºC (77ºF)

Inactive ingredients

docusate sodium, fumaric acid, lactose monohydrate, potassium chloride, sodium benzoate

Questions or comments?

1-800-321-7178

PRINCIPAL DISPLAY PANEL

Headache Powders